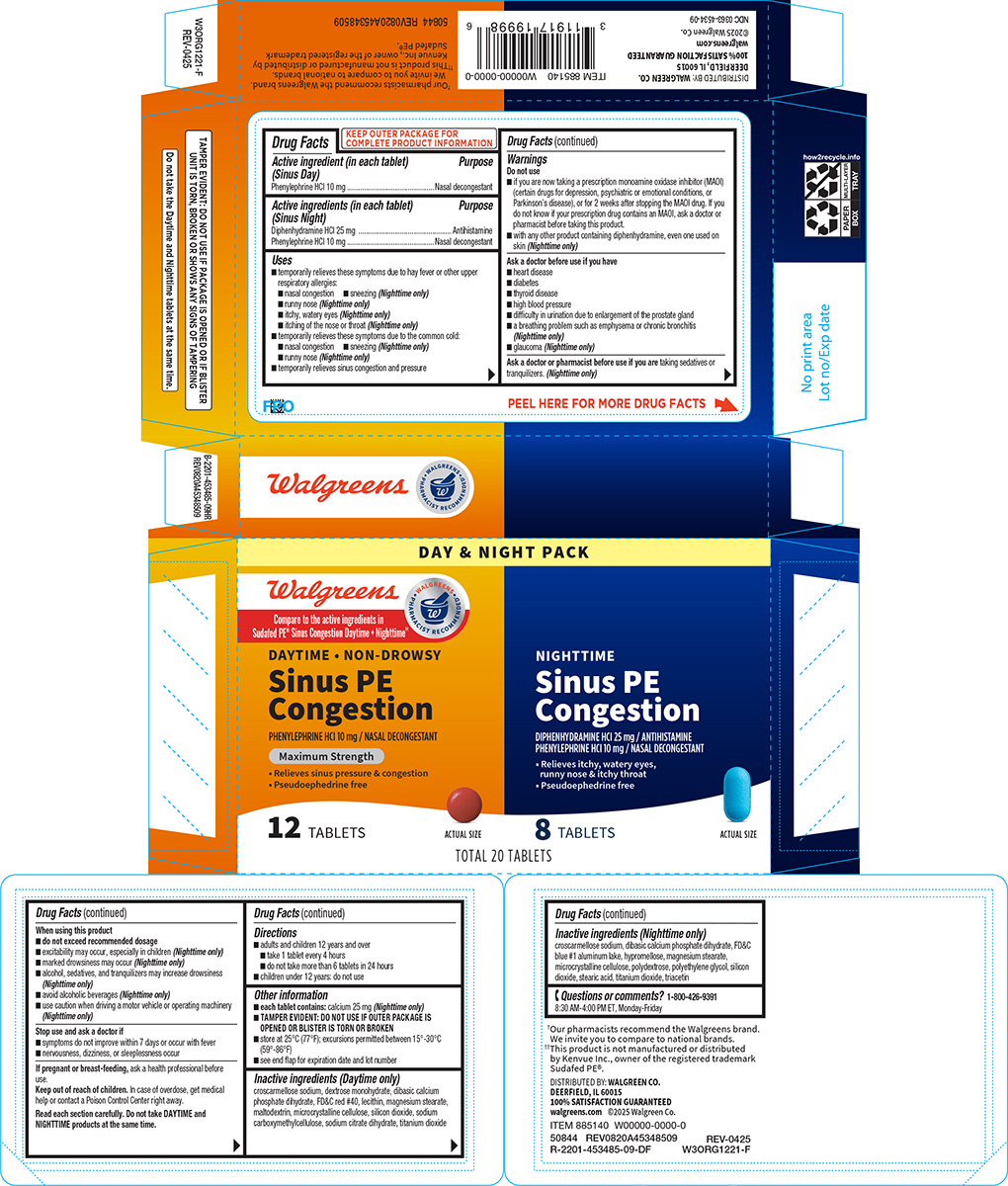 DRUG LABEL: Sinus PE Congestion
NDC: 0363-4534 | Form: KIT | Route: ORAL
Manufacturer: Walgreen Company
Category: otc | Type: HUMAN OTC DRUG LABEL
Date: 20251210

ACTIVE INGREDIENTS: PHENYLEPHRINE HYDROCHLORIDE 10 mg/1 1; DIPHENHYDRAMINE HYDROCHLORIDE 25 mg/1 1; PHENYLEPHRINE HYDROCHLORIDE 10 mg/1 1
INACTIVE INGREDIENTS: CROSCARMELLOSE SODIUM; DEXTROSE MONOHYDRATE; DIBASIC CALCIUM PHOSPHATE DIHYDRATE; FD&C RED NO. 40; LECITHIN, SOYBEAN; MAGNESIUM STEARATE; MALTODEXTRIN; MICROCRYSTALLINE CELLULOSE; SILICON DIOXIDE; CARBOXYMETHYLCELLULOSE SODIUM, UNSPECIFIED; TRISODIUM CITRATE DIHYDRATE; TITANIUM DIOXIDE; CROSCARMELLOSE SODIUM; DIBASIC CALCIUM PHOSPHATE DIHYDRATE; FD&C BLUE NO. 1 ALUMINUM LAKE; HYPROMELLOSE, UNSPECIFIED; MAGNESIUM STEARATE; MICROCRYSTALLINE CELLULOSE; POLYDEXTROSE; POLYETHYLENE GLYCOL, UNSPECIFIED; SILICON DIOXIDE; STEARIC ACID; TITANIUM DIOXIDE; TRIACETIN

Walgreens 44-453485-Sinus PE Congestion

Active ingredient (in each tablet) (Sinus Day)

Phenylephrine HCl 10 mg

Purpose

Nasal decongestant

Active ingredients (in each tablet) (Sinus Night)

Diphenhydramine HCl 25 mg
Phenylephrine HCl 10 mg

Purpose

Antihistamine
Nasal decongestant

Uses

- temporarily relieves these symptoms due to hay fever or other upper respiratory allergies:
  - nasal congestion
  - sneezing (Nighttime only)
  - runny nose (Nighttime only)
  - itchy, watery eyes (Nighttime only)
  - itching of the nose or throat (Nighttime only)
- temporarily relieves these symptoms due to the common cold:
  - nasal congestion
  - sneezing (Nighttime only)
  - runny nose (Nighttime only)
- temporarily relieves sinus congestion and pressure

Warnings

Do not use

- if you are now taking a prescription monoamine oxidase inhibitor (MAOI) (certain drugs for depression, psychiatric or emotional conditions, or Parkinson’s disease), or for 2 weeks after stopping the MAOI drug. If you do not know if your prescription drug contains an MAOI, ask a doctor or pharmacist before taking this product.
- with any other product containing diphenhydramine, even one used on skin (Nighttime only)

Ask a doctor before use if you have

- heart disease
- diabetes
- thyroid disease
- high blood pressure
- difficulty in urination due to enlargement of the prostate gland
- a breathing problem such as emphysema or chronic bronchitis (Nighttime only)
- glaucoma (Nighttime only)

Ask a doctor or pharmacist before use if you are

taking sedatives or tranquilizers. (Nighttime only)

When using this product

- do not exceed recommended dosage
- excitability may occur, especially in children (Nighttime only)
- marked drowsiness may occur (Nighttime only)
- alcohol, sedatives, and tranquilizers may increase drowsiness (Nighttime only)
- avoid alcoholic beverages (Nighttime only)
- use caution when driving a motor vehicle or operating machinery (Nighttime only)

Stop use and ask a doctor if

- symptoms do not improve within 7 days or occur with fever
- nervousness, dizziness, or sleeplessness occur

If pregnant or breast-feeding,

ask a health professional before use.

Keep out of reach of children.

In case of overdose, get medical help or contact a Poison Control Center right away.

Read each section carefully. Do not take DAYTIME and NIGHTTIME products at the same time.

Directions

- adults and children 12 years and over
  - take 1 tablet every 4 hours
  - do not take more than 6 tablets in 24 hours
- children under 12 years: do not use

Other information

- each tablet contains: calcium 25 mg (Nighttime only)
- TAMPER EVIDENT: DO NOT USE IF OUTER PACKAGE IS OPENED OR BLISTER IS TORN OR BROKEN
- store at 25°C (77°F); excursions permitted between 15°-30°C (59°-86°F)
- see end flap for expiration date and lot number

Inactive ingredients (Daytime only)

croscarmellose sodium, dextrose monohydrate, dibasic calcium phosphate dihydrate, FD&C red #40, lecithin, magnesium stearate, maltodextrin, microcrystalline cellulose, silicon dioxide, sodium carboxymethylcellulose, sodium citrate dihydrate, titanium dioxide

Inactive ingredients (Nighttime only)

croscarmellose sodium, dibasic calcium phosphate dihydrate, FD&C blue #1 aluminum lake, hypromellose, magnesium stearate, microcrystalline cellulose, polydextrose, polyethylene glycol, silicon dioxide, stearic acid, titanium dioxide, triacetin

Questions or comments?

1-800-426-9391 8:30 AM-4:00 PM ET, Monday-Friday

Principal display panel

DAY & NIGHT PACK

Walgreens

• WALGREENS •
PHARMACIST RECOMMENDED†

Compare to the active ingredients in
Sudafed PE® Sinus Congestion Daytime + Nighttime††

DAYTIME • NON-DROWSY

Sinus PE
Congestion

PHENYLEPHRINE HCI 10 mg / NASAL DECONGESTANT

Maximum Strength

• Relieves sinus pressure & congestion
• Pseudoephedrine free

12 TABLETS

ACTUAL SIZE

NIGHTTIME

Sinus PE
Congestion

DIPHENHYDRAMINE HCl 25 mg / ANTIHISTAMINE
PHENYLEPHRINE HCl 10 mg / NASAL DECONGESTANT

• Relieves itchy, water eyes,
runny nose & itchy throat
• Pseudoephedrine free

8 TABLETS

ACTUAL SIZE

TOTAL 20 TABLETS

TAMPER EVIDENT: DO NOT USE IF PACKAGE IS OPENED OR IF BLISTER
UNIT IS TORN, BROKEN OR SHOWS ANY SIGNS OF TAMPERING

Do not take the Daytime and Nighttime tablets at the same time.

†Our pharmacists recommend the Walgreens brand.
We invite you to compare to national brands.

††This product is not manufactured or distributed by
Kenvue Inc., owner of the registered trademark
Sudafed PE®.

50844 REV0820A45348509

DISTRIBUTED BY: WALGREEN CO.
DEERFIELD, IL 60015
100% SATISFACTION GUARANTEED
walgreens.com
©2025 Walgreen Co.
NDC 0363-4534-09

REV-0425
W3ORG1221-F

Walgreens 44-453485